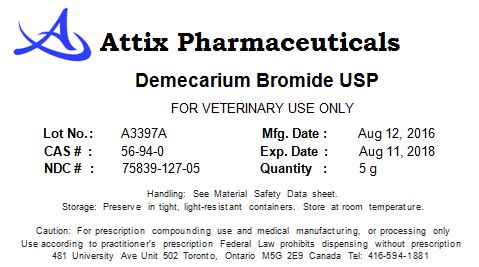 DRUG LABEL: Demecarium Bromide
NDC: 75839-127 | Form: POWDER
Manufacturer: Attix Pharmaceuticals Inc
Category: other | Type: BULK INGREDIENT
Date: 20180410

ACTIVE INGREDIENTS: DEMECARIUM BROMIDE 10 g/10 g

Demecarium Bromide